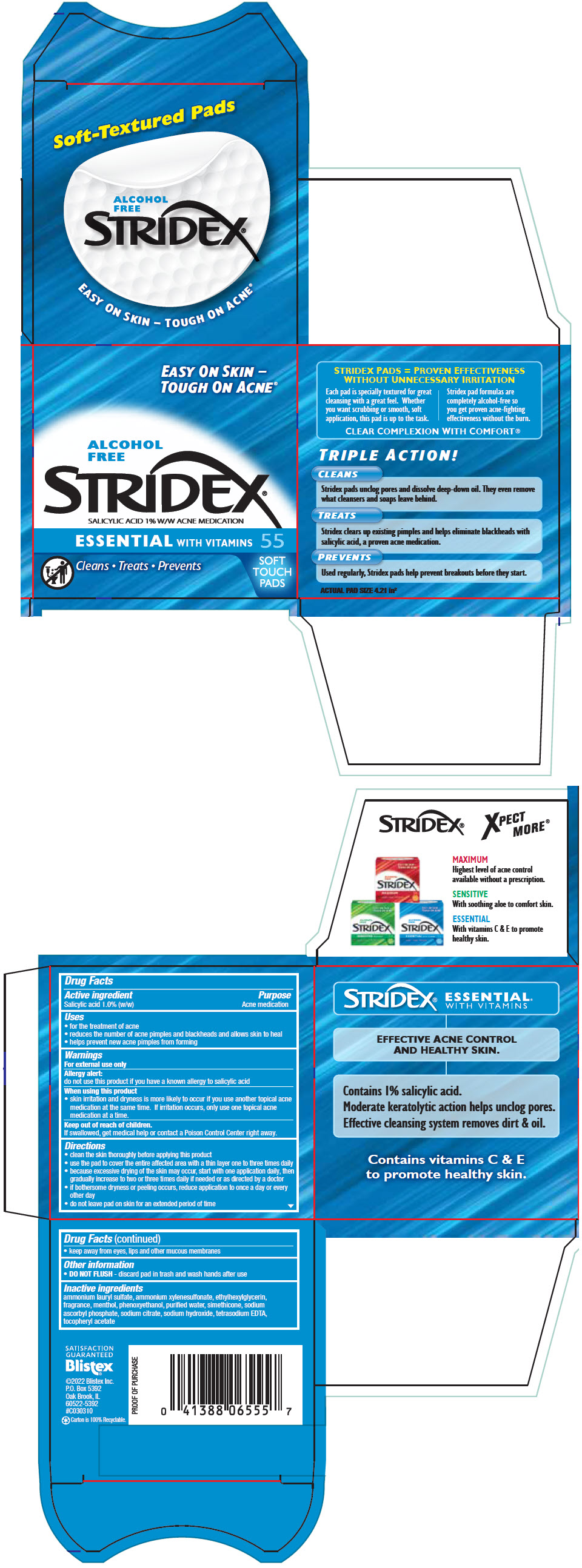 DRUG LABEL: Stridex Essential
NDC: 10157-2119 | Form: LIQUID
Manufacturer: Blistex Inc
Category: otc | Type: HUMAN OTC DRUG LABEL
Date: 20241213

ACTIVE INGREDIENTS: Salicylic Acid 1 g/100 mL
INACTIVE INGREDIENTS: Water; Ammonium Xylenesulfonate; Ammonium Lauryl Sulfate; SODIUM CITRATE, UNSPECIFIED FORM; Phenoxyethanol; Ethylhexylglycerin; Sodium Hydroxide; MENTHOL, UNSPECIFIED FORM; SILICON DIOXIDE; Sodium Ascorbyl Phosphate; EDETATE SODIUM; .ALPHA.-TOCOPHEROL ACETATE

Stridex® Essential

Drug Facts

Active ingredient

Salicylic acid 1.0% (w/w)

Purpose

Acne medication

Uses

- for the treatment of acne
- reduces the number of acne pimples and blackheads and allows skin to heal
- helps prevent new acne pimples from forming

Warnings

For external use only

Allergy alert

do not use this product if you have a known allergy to salicylic acid

When using this product

- skin irritation and dryness is more likely to occur if you use another topical acne medication at the same time. If irritation occurs, only use one topical acne medication at a time.

Keep out of reach of children.

If swallowed, get medical help or contact a Poison Control Center right away.

Directions

- clean the skin thoroughly before applying this product
- use the pad to cover the entire affected area with a thin layer one to three times daily
- because excessive drying of the skin may occur, start with one application daily, then gradually increase to two or three times daily if needed or as directed by a doctor
- if bothersome dryness or peeling occurs, reduce application to once a day or every other day
- do not leave pad on skin for an extended period of time
- keep away from eyes, lips and other mucous membranes

Other information

- DO NOT FLUSH - discard pad in trash and wash hands after use

Inactive ingredients

ammonium lauryl sulfate, ammonium xylenesulfonate, ethylhexylglycerin, fragrance, menthol, phenoxyethanol, purified water, simethicone, sodium ascorbyl phosphate, sodium citrate, sodium hydroxide, tetrasodium EDTA, tocopheryl acetate

PRINCIPAL DISPLAY PANEL - 55 Pad Jar Carton

EASY ON SKIN –
TOUGH ON ACNE®

ALCOHOL
FREE

STRIDEX®
SALICYLIC ACID 1% W/W ACNE MEDICATION

ESSENTIAL WITH VITAMINS

55
SOFT
TOUCH
PADS

Cleans • Treats • Prevents